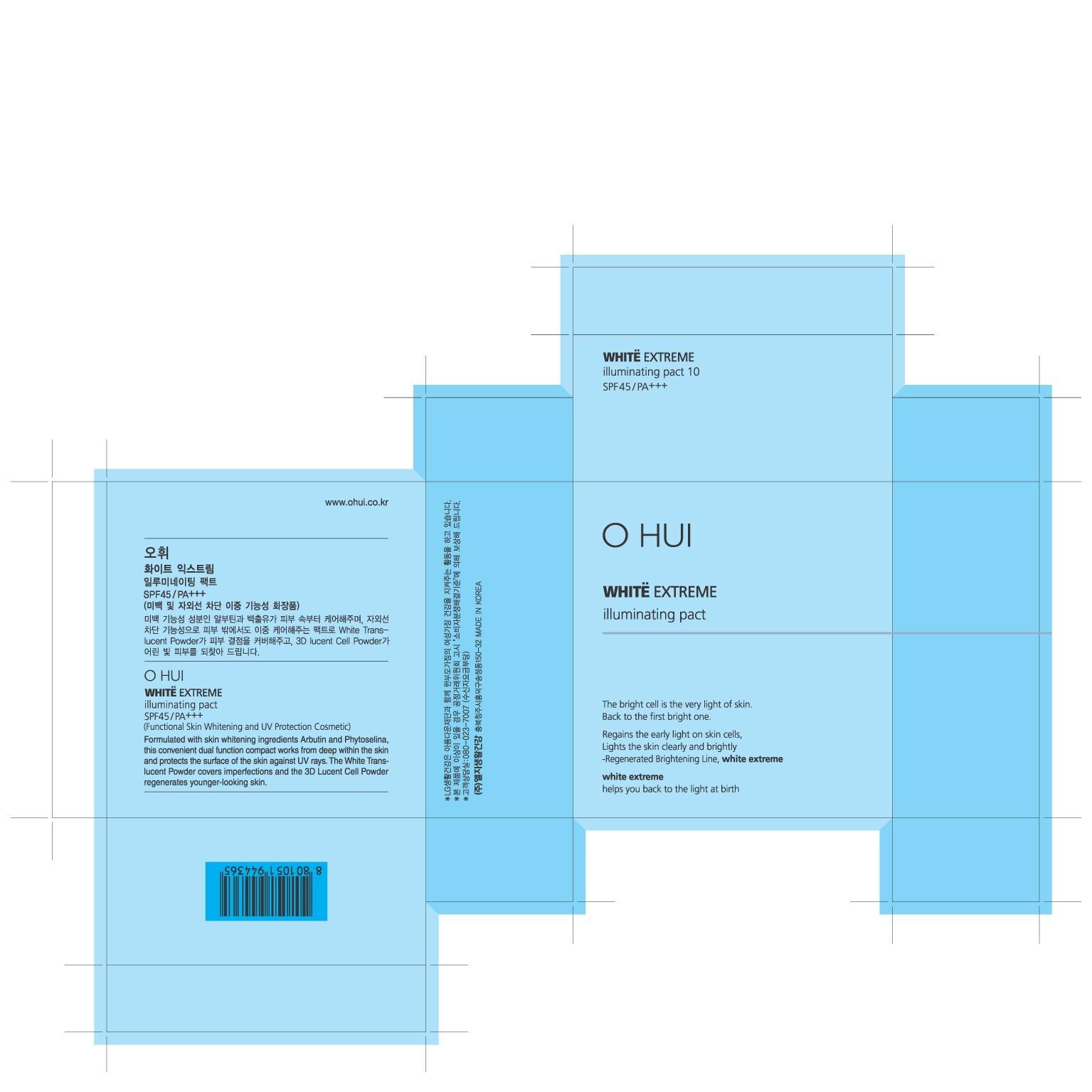 DRUG LABEL: OHUI White Extreme Illuminating Pact No.10
NDC: 53208-533 | Form: POWDER
Manufacturer: LG Household and Healthcare, Inc.
Category: otc | Type: HUMAN OTC DRUG LABEL
Date: 20120514

ACTIVE INGREDIENTS: TITANIUM DIOXIDE 9.84 g/100 g; OCTINOXATE 4.5 g/100 g; ARBUTIN 2 g/100 g; ATRACTYLODES JAPONICA ROOT OIL 0.1 g/100 g
INACTIVE INGREDIENTS: TALC; TRIETHOXYCAPRYLYLSILANE; BORON NITRIDE; DIMETHICONE; MICA; TALC; ALUMINUM HYDROXIDE; STEARIC ACID; MAGNESIUM MYRISTATE; SILICON DIOXIDE; TRIETHYLHEXANOIN; FERRIC OXIDE YELLOW; SILICON DIOXIDE; WATER; ALCOHOL; METHYLPARABEN; MAGNESIUM STEARATE; FERRIC OXIDE RED; FERROSOFERRIC OXIDE; PROPYLPARABEN; DIAMOND; COPPER; BUTYLENE GLYCOL; POLYSORBATE 20; PALMITOYL OLIGOPEPTIDE

Drug Fact

ACTIVE INGREDIENT

TITANIUM DIOXIDE 9.84%
OCTINOXATE 4.5%
ARBUTIN 2%
ATRACTYLODES JAPONICA ROOT OIL 0.1%

WARNINGS AND PRECAUTIONS

For external use only

Keep out of reach of children. Is swallowed, get medical help or contact a
Poison Control Center right away.

WHEN USING

Keep out of eyes. Rinse with water to remove

Stop use if a rash or irritation develops and lasts.

PACKAGE LABEL

OHUI White Extreme Illuminating Pact #10